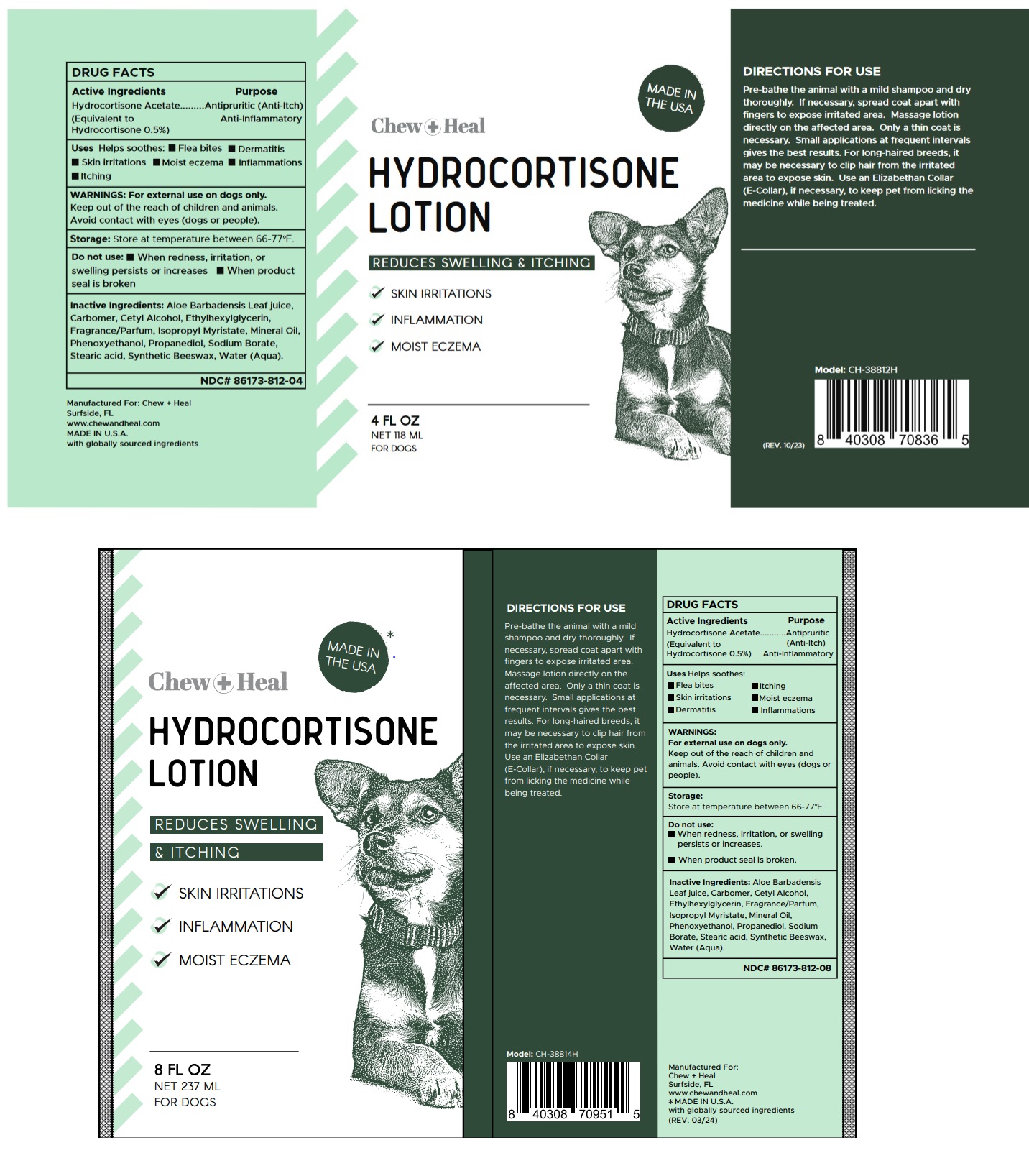 DRUG LABEL: Chew Plus Heal HYDROCORTISONE
NDC: 86173-812 | Form: LOTION
Manufacturer: Click Industries LLC
Category: animal | Type: OTC ANIMAL DRUG LABEL
Date: 20240305

ACTIVE INGREDIENTS: HYDROCORTISONE 0.5 g/100 mL
INACTIVE INGREDIENTS: ALOE VERA LEAF; CARBOMER HOMOPOLYMER TYPE B (ALLYL SUCROSE CROSSLINKED); CETYL ALCOHOL; ETHYLHEXYLGLYCERIN; ISOPROPYL MYRISTATE; MINERAL OIL; PHENOXYETHANOL; PROPANEDIOL; SODIUM BORATE; STEARIC ACID; SYNTHETIC BEESWAX; WATER

Chew + Heal HYDROCORTISONE LOTION

DRUG FACTS

Active Ingredients

Hydrocortisone acetate

(Equivalent to Hydrocortisone 0.5%)

Purpose

Antipruritic (Anti-Itch)

Anti-Inflammatory

Uses

Helps soothes: • Flea bites • Dermatitis • Skin irritations • Moist eczema • Inflammations • Itching

WARNINGS:

For external use on dogs only.
Keep out of the reach of children and animals.
Avoid contact with eyes (dogs or people)

DIRECTIONS FOR USE

Pre-bathe the animal with a mild shampoo and dry thoroughly. If necessary, spread coat apart with fingers to expose irritated area. Massage lotion directly on the affected area. Only a thin coat is necessary. Small applications at frequent intervals gives the best results. For long-haired breeds, it may be necessary to clip hair from the irritated area to expose skin. Use an Elizabethan Collar (E-Collar), if necessary, to keep pet from licking the medicine while being treated.

Storage:

Store at temperature between 66-77°F.

Do not use:

• When redness, irritation, or swelling persists or increases • When product seal is broken

Inactive Ingredients:

Aloe Barbadensis Leaf juice, Carbomer, Cetyl Alcohol, Ethylhexylglycerin, Fragrance/Parfum, Isopropyl Myristate, Mineral Oil, Phenoxyethanol, Propanediol, Sodium Borate, Stearic acid, Synthetic Beeswax, Water (Aqua)

REDUCES SWELLING & ITCHING

FOR DOGS

Manufactured For: Chew + Heal
Surfside, FL
www.chewandheal.com
MADE IN U.S.A
with globally sourced ingredients